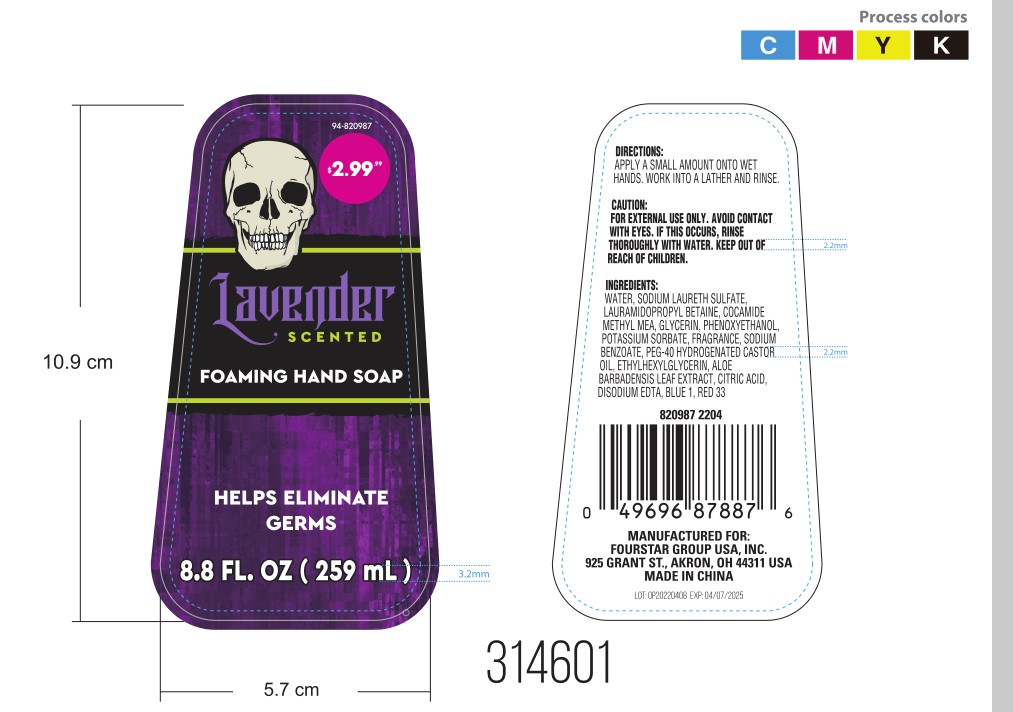 DRUG LABEL: Foaming Hand
NDC: 41366-056 | Form: LIQUID
Manufacturer: Zhejiang Meimi Technology Co., Ltd.
Category: otc | Type: HUMAN OTC DRUG LABEL
Date: 20251206

ACTIVE INGREDIENTS: COCOYL METHYL MONOETHANOLAMINE 1.2 g/100 mL; LAURAMIDOPROPYL BETAINE 5 g/100 mL
INACTIVE INGREDIENTS: POLYOXYL 40 HYDROGENATED CASTOR OIL; ALOE VERA LEAF; SODIUM BENZOATE; ETHYLHEXYLGLYCERIN; D&C RED NO. 33; WATER; SODIUM LAURETH SULFATE; PHENOXYETHANOL; GLYCERIN; POTASSIUM SORBATE; ACONITIC ACID; EDETATE DISODIUM ANHYDROUS; FD&C BLUE NO. 1; LAVANDULA X INTERMEDIA FLOWER

Zhejiang Meimi Technology Co., Ltd.
Foaming Hand Soap
41366-056-01

Active Ingredient(s)

Sodium Laureth Sulfate, Cocamide Methyl MEA.

Warnings

- FOR EXTERNAL USE ONLY.
- AVOID CONTACT WITH EYES. IF THIS OCCURS, RINSE THOROUGELY WITH WATER.
- KEEP OUT OF REACH OF CHILDREN.

Keep out of reach of children.

Directions

APPLYASMALL AMOUNT ONTO WET HANDS. WORK INTO A LATHER AND RINSE.

Inactive ingredients

WATER, LAURAMIDOPROPL BETAINE, GLYCERIN, PHENOXYETHANOL, POTASSIUM SORBATE, FRAGRANCE, SODIUM
BENZOATE, PEG-40 HYDROGENATED CASTOR OIL, ETHYLHEXYLGLYCERIN, ALOE BARBADENSIS LEAF EXTRACT, CITRIC ACID, DISODIUM EDTA, BLUE 1, RED 33.

PURPOSE

Antimicrobial

INDICATIONS AND USAGE

APPLYASMALL AMOUNT ONTO WET HANDS. WORK INTO A LATHER AND RINSE.

Package Label - Principal Display Panel

259 mL in 1 BOTTLE

NDC: 41366-056-01